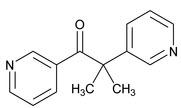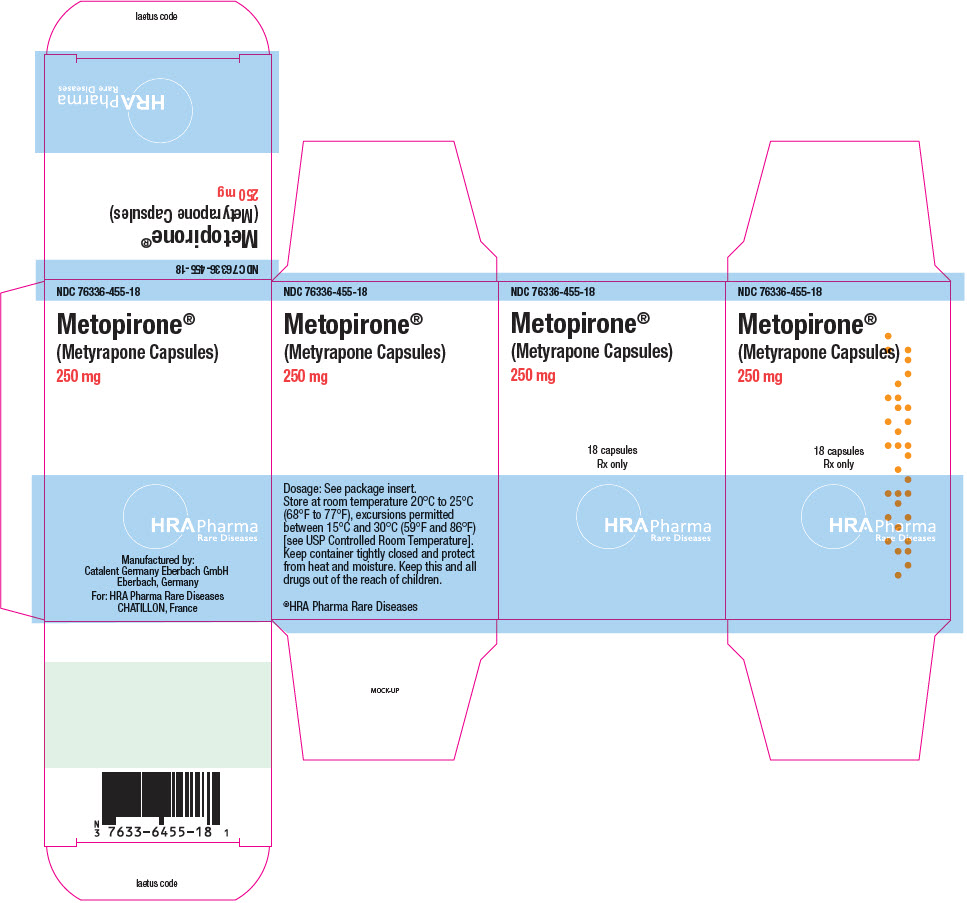 DRUG LABEL: Metopirone
NDC: 76336-455 | Form: CAPSULE, GELATIN COATED
Manufacturer: HRA Pharma Rare Diseases
Category: prescription | Type: HUMAN PRESCRIPTION DRUG LABEL
Date: 20260107

ACTIVE INGREDIENTS: METYRAPONE 250 mg/1 1
INACTIVE INGREDIENTS: POLYETHYLENE GLYCOL 400; POLYETHYLENE GLYCOL 4000; GLYCERIN; SODIUM ETHYLPARABEN; 4-ACETYLANISOLE; GELATIN, UNSPECIFIED; PROPYLPARABEN SODIUM; ETHYL VANILLIN; TITANIUM DIOXIDE; WATER

HIGHLIGHTS OF PRESCRIBING INFORMATION

These highlights do not include all the information needed to use METOPIRONE safely and effectively. See full prescribing information for METOPIRONE.
METOPIRONE®(metyrapone capsules), for oral use
Initial U.S. Approval: 1961

RECENT MAJOR CHANGES

Indications and Usage (1) | 09/2022
Dosage and Administration, Single-Dose Short Test (2.2) | 09/2022

1 INDICATIONS AND USAGE

Metopirone is indicated, in combination with other diagnostic tests, for the diagnosis of adrenal insufficiency in adult and pediatric patients. (1)

2 DOSAGE AND ADMINISTRATION

- Single-Dose Short Test: 30 mg/kg at midnight (2.2)

3 DOSAGE FORMS AND STRENGTHS

Capsules: 250 mg (3)

4 CONTRAINDICATIONS

- In patients with adrenal cortical insufficiency (4)
- Hypersensitivity to Metopirone or to any of its excipients (4)

5 WARNINGS AND PRECAUTIONS

- Adrenal Insufficiency: May induce acute adrenal insufficiency. Ability of adrenals to respond to exogenous ACTH should be demonstrated before Metopirone is employed as a test (5.1)
- Dizziness and Sedation: May cause dizziness and sedation. Patients should not drive or operate machinery until these effects have passed (5.2)

6 ADVERSE REACTIONS

Adverse reactions include: hypotension, nausea, vomiting, abdominal discomfort or pain, headache, dizziness, sedation, allergic rash, leukopenia, anemia, and/or thrombocytopenia. (6)

To report SUSPECTED ADVERSE REACTIONS, contact Direct Success Inc. at 844-597-6373 or FDA at 1-800-FDA-1088 or www.fda.gov/medwatch.

7 DRUG INTERACTIONS

- Anticonvulsants, psychotropic, hormone preparations, corticosteroids, antithyroid agents, cyproheptadine: may affect the results of the metyrapone test. (7.1)
- Acetaminophen: Avoid concomitant use with Metopirone. (7.2)

FULL PRESCRIBING INFORMATION

1 INDICATIONS AND USAGE

Metopirone is indicated, in combination with other diagnostic tests, for the diagnosis of adrenal insufficiency in adult and pediatric patients.

2 DOSAGE AND ADMINISTRATION

2.1 Important Information Before Conducting Metopirone Testing

Stop drugs affecting pituitary or adrenocortical function before administration of Metopirone in accordance with half-life of the drugs (consider at least 5 half-lives to avoid any interference with Metopirone testing). [see Drug Interactions (7.1)] .

Assess ability of patient's adrenals to respond to exogenous ACTH before Metopirone is employed as a test [see Warnings and Precautions (5.1)] .

2.2 Single-Dose Short Test- Recommended Dose and Interpretation

This test, usually given on an outpatient basis, determines plasma 11-desoxycortisol and/or ACTH levels after a single dose of Metopirone. Patients with suspected adrenocortical insufficiency based on the test results previously performed should be hospitalized overnight as a precautionary measure (see Warnings and Precaution (5.1)).

Recommended Dose

In adult and pediatric patients, the recommended single dose is 30 mg/kg (maximum 3 grams of Metopirone) administered at midnight with milk/yogurt or snack. The blood sample for the assay is taken early the following morning (7:30-8:00 a.m.). After the blood sample is collected, a prophylactic dose of glucocorticoid may be considered for patients with high risk for acute adrenal insufficiency.

Interpretation of 11‑desoxycortisol and ACTH Levels After Metopirone Administration

Approximately 8 hours after administration of Metopirone, evaluate the values of ACTH and 11-desoxycortisol. Normal values will depend on the method used to determine ACTH and 11‑desoxycortisol levels. An intact HPA axis function is generally indicated by an increase in 11‑desoxycortisol to over 70 mcg/L. Because of an overlap between a normal ACTH response and an abnormal ACTH response, the ACTH response alone cannot be used to distinguish between healthy individuals and those with adrenal insufficiency.

3 DOSAGE FORMS AND STRENGTHS

Capsules: Metopirone 250 mg soft gelatin, white to yellowish‑white, oblong, opaque, imprinted with "HRA" on one side in red ink.

4 CONTRAINDICATIONS

Metopirone is contraindicated in patients with adrenal cortical insufficiency or hypersensitivity to Metopirone or to any of its excipients.

5 WARNINGS AND PRECAUTIONS

5.1 Adrenal Insufficiency

Metopirone may induce acute adrenal insufficiency in patients with reduced adrenal secretory capacity, as well as in patients with global pituitary insufficiency. The test should be performed in the hospital with close monitoring in case of suspected adrenal insufficiency.

Ability of adrenals to respond to exogenous ACTH should be demonstrated before Metopirone is employed as a test.

In the presence of hypo‑ or hyperthyroidism, response to the Metopirone test may be subnormal.

If adrenocortical or anterior pituitary function is more severely compromised than indicated by the results of the test, Metopirone may trigger adrenal insufficiency. This can be corrected by giving appropriate doses of corticosteroids.

5.2 Dizziness and Sedation

Metopirone may cause dizziness and sedation. Patients should not drive or operate machinery until these effects have passed.

6 ADVERSE REACTIONS

The following adverse reactions associated with the use of Metopirone were identified in clinical trials or postmarketing reports. Because these reactions were reported voluntarily from a population of uncertain size, it is not always possible to reliably estimate their frequency or establish a causal relationship to drug exposure.

- Cardiovascular System:Hypotension
- Gastrointestinal System:Nausea, vomiting, abdominal discomfort or pain
- Central Nervous System:Headache, dizziness, sedation
- Dermatologic System:Allergic rash
- Hematologic System:Leukopenia, anemia, and/or thrombocytopenia

7 DRUG INTERACTIONS

7.1 Effect of Other Drugs on Metopirone

Anticonvulsants, psychotropic drugs, hormone preparations, corticosteroids, antithyroid agents and cyproheptadine may affect the results of the Metopirone test.

If these drugs cannot be withdrawn, the necessity of carrying out the Metopirone test should be reviewed.

7.2 Effect of Metopirone on Other Drugs

Acetaminophen

Metopirone inhibits the glucuronidation of acetaminophen, which may decrease elimination of acetaminophen and lead to increased risk of adverse reactions related to acetaminophen.

Avoid concomitant use of Metopirone with acetaminophen.

8 USE IN SPECIFIC POPULATIONS

8.1 Pregnancy

Risk Summary

Available data from published case series and reports on Metopirone use in pregnant females are insufficient to identify a drug-associated risk of major birth defects or miscarriage. Metyrapone crosses the placenta and may decrease fetal cortisol production (see Data) . Animal reproductive studies have not been conducted with metyrapone. Metyrapone can decrease reproductive hormones by targeting adrenal androgenesis.

Data

Human Data

The Metopirone test was administered to pregnant women in their second and third trimester of pregnancy and evidence was found that the fetal pituitary responded to the enzymatic block. Transplacental transfer of Metopirone has been shown in humans and the drug can impair the biosynthesis of fetal and placental steroids. There are a few published reports of low cortisol levels at birth in infants exposed in utero following chronic use of metyrapone in pregnant females.

8.2 Lactation

Risk Summary

Metyrapone and its active metabolite, metyrapol, are present in human milk. There are no available data on the effects of metyrapone on the breastfed infant or the effects on milk production. The developmental and health benefits of breastfeeding should be considered along with the mother's clinical need for Metopirone and any potential adverse effects on the breastfed infant from Metopirone or from the underlying maternal condition.

8.4 Pediatric Use

Metopirone is indicated, in combination with other diagnostic tests, for the diagnosis of adrenal insufficiency in pediatric patients [See Dosage and Administration (2.1)].

8.5 Geriatric Use

Clinical studies of Metopirone did not include sufficient numbers of patients 65 years of age and older to determine whether they respond differently from younger adult patients.

Other reported clinical experience has not identified differences in responses between patients 65 years of age and older and younger adult patients.

8.6 Hepatic Impairment

Patients with cirrhosis may have an impaired response to Metopirone.

10 OVERDOSAGE

Death occurred in a child after two doses of Metopirone 2 g.

Signs and Symptoms of Overdosage

The clinical picture of overdosage with Metopirone is characterized by gastrointestinal symptoms and by signs of acute adrenal insufficiency.

- Cardiovascular System: Cardiac arrhythmias, hypotension, dehydration.
- Nervous System and Muscles: Anxiety, confusion, weakness, impairment of consciousness.
- Gastrointestinal System:Nausea, vomiting, epigastric pain, diarrhea.
- Laboratory Findings:Hyponatremia, hypochloremia, hyperkalemia.

In patients under treatment with insulin or oral antidiabetics, the signs and symptoms of acute overdosage with Metopirone may be aggravated or modified.

Treatment and Management of Overdosage

There is no specific antidote for Metopirone overdosage. Immediate treatment is essential in the management of Metopirone overdose.

Treatment with activated charcoal may be considered if the overdose has been taken within 1 hour. In addition to general measures, hydrocortisone should be administered at once, together with IV saline and glucose. This should be repeated as necessary in accordance with the patient's clinical condition.

For a few days blood pressure and fluid and electrolyte balance should be monitored.

Consult with a regional poison control center (1-800-222-1222) for additional treatment recommendations.

11 DESCRIPTION

Metopirone (metyrapone capsules) is an adrenal steroid synthesis inhibitor, available as 250‑mg capsules for oral administration. Its chemical name is 2‑methyl‑1, 2‑di‑3‑pyridyl‑1‑propanone, and its structural formula is

Metyrapone is a white to light amber, fine, crystalline powder, having a characteristic odor. It is sparingly soluble in water, and soluble in methanol and in chloroform. It forms water‑soluble salts with acids. Its molecular weight is 226.27.

Inactive Ingredients: Ethyl vanillin, gelatin, glycerol, macrogol 400, macrogol 4000, paramethoxy acetophenone, purified water, sodium ethyl parahydroxybenzoate, sodium propyl parahydroxybenzoate, titanium dioxide, + red ink (aluminum chloride hexahydrate, carminic acid, hypromellose, propylene glycol, sodium hydroxide).

12 CLINICAL PHARMACOLOGY

12.1 Mechanism of Action

The pharmacological effect of Metopirone is to reduce cortisol and corticosterone production by inhibiting the 11-beta-hydroxylation reaction in the adrenal cortex. Removal of the strong inhibitory feedback mechanism exerted by cortisol results in an increase in adrenocorticotropic hormone (ACTH) production by the pituitary. With continued blockade of the enzymatic steps leading to production of cortisol and corticosterone, there is a marked increase in adrenocortical secretion of their immediate precursors, 11-desoxycortisol and desoxycorticosterone, which are weak suppressors of ACTH release, and a corresponding elevation of these steroids in the plasma and of their metabolites in the urine. These metabolites are readily determined by measuring urinary 17‑hydroxycorticosteroids (17-OHCS) or 17-ketogenic steroids (17-KGS). Because of these actions, Metopirone is used as a diagnostic test, with urinary 17-OHCS measured as an index of pituitary ACTH responsiveness. Metopirone may also suppress biosynthesis of aldosterone, resulting in a mild natriuresis.

12.2 Pharmacodynamics

Metopirone exposure-response relationships and the time course of pharmacodynamic response are unknown.

12.3 Pharmacokinetics

The mean Cmaxof metyrapone following a single 750 mg is 3.7 mcg/mL falling to 0.5 mcg/mL 4 hours after administration.

Absorption

The time to peak plasma concentration of metyrapone is approximately 1 hour after oral administration.

Elimination

The mean (± SD) terminal elimination half‑lives of metyrapone and its active metabolite metyrapol are 1.9 (± 0.7) hours and approximately 4 hours, respectively.

Metabolism

Metyrapone is reduced to metyrapol, an active alcohol metabolite. Both metyrapone and metyrapol are conjugated with glucuronide.

Eight hours after a single oral dose, the ratio of metyrapone to its active metabolite metyrapol in plasma is 1:1.5.

Excretion

Following administration of metyrapone 750 mg every 4 hours, approximately 5.3% of the dose was excreted in urine as unchanged and 38.5% as its active metabolite metyrapol within 72 hours after the first dose.

13 NONCLINICAL TOXICOLOGY

13.1 Carcinogenesis, Mutagenesis, Impairment of Fertility

Carcinogenesis

Long‑term animal carcinogenicity studies have not been conducted with Metopirone.

Mutagenesis

Metyrapone was not mutagenic with or without metabolic activation in bacterial mutagenicity tests.

Impairment of Fertility

No studies have been conducted to assess the effect of Metopirone on fertility.

16 HOW SUPPLIED/STORAGE AND HANDLING

How Supplied

Metopirone (metyrapone capsules) are supplied as 250 mg soft gelatin, white to yellowish‑white, oblong, opaque capsules, imprinted with "HRA" on one side in red ink.

Bottle of 18 capsules: NDC 76336-455-18

Storage and Handling

Store Metopirone bottles at room temperature 20°C to 25°C (68°F to 77°F), excursions permitted between 15°C and 30°C (59°F and 86°F) [see USP Controlled Room Temperature].

Keep container tightly closed and protect from heat and moisture.

17 PATIENT COUNSELING INFORMATION

Advise patient to read the FDA-approved labeling (Patient Information).

Advise patient that Metopirone may induce acute adrenal insufficiency (nausea, vomiting, abdominal pain, hypotension) [see Warnings and Precautions (5.1)] .

Advise patient that Metopirone may cause dizziness and sedation. Advise patients not to drive or operate machinery until these effects have passed [see Warnings and Precautions (5.2)] .

Manufactured by:
Catalent Germany Eberbach GmbH
Eberbach, Germany

For:
HRA Pharma Rare Diseases
CHATILLON, France

© 2022 HRA Pharma Rare Diseases | Metopirone is a registered trademark of HRA Pharma Rare Diseases

Address medical inquiries to:
Direct Success Inc.
1710 Hwy 34
Farmingdale, NJ 07727
1-844-597-6373
Fax: 1-855-674-6767

PRINCIPAL DISPLAY PANEL - 250 mg Bottle Carton

NDC 76336-455-18

Metopirone®
(Metyrapone Capsules)
250 mg

18 capsules
Rx only

HRA Pharma
Rare Diseases